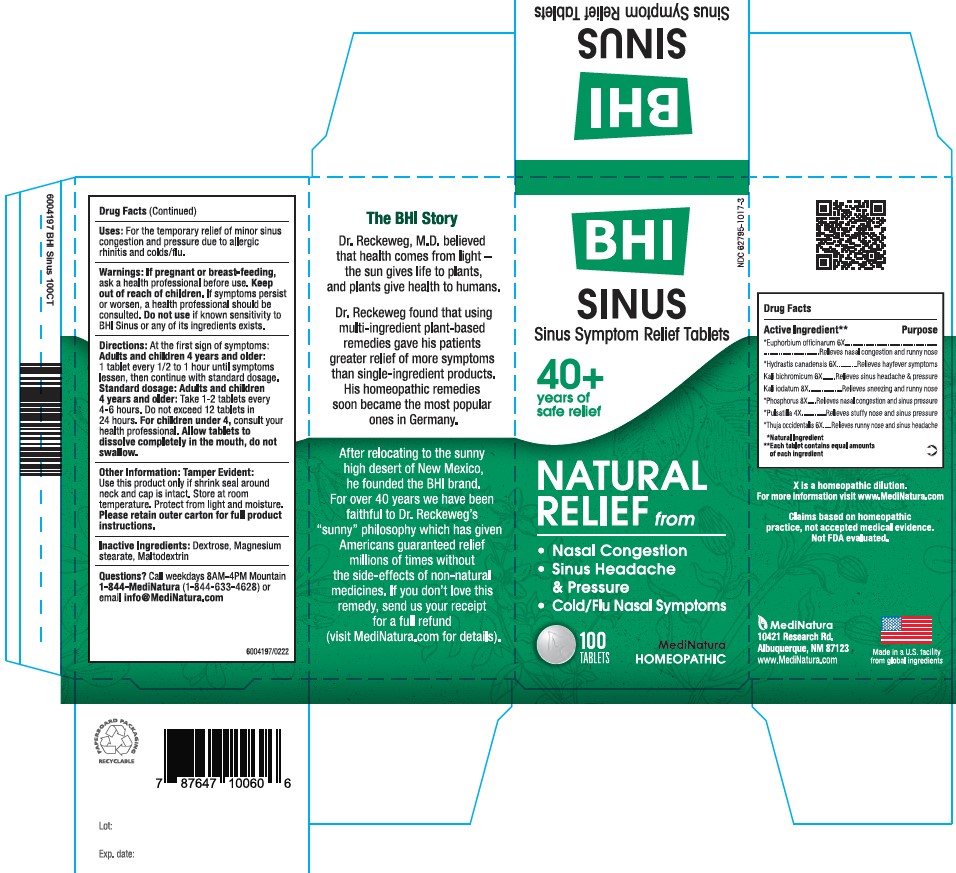 DRUG LABEL: BHI Sinus
NDC: 62795-1017 | Form: TABLET
Manufacturer: MediNatura Inc
Category: homeopathic | Type: HUMAN OTC DRUG LABEL
Date: 20220808

ACTIVE INGREDIENTS: EUPHORBIA RESINIFERA RESIN 6 [hp_X]/1 1; GOLDENSEAL 6 [hp_X]/1 1; POTASSIUM DICHROMATE 6 [hp_X]/1 1; POTASSIUM IODIDE 8 [hp_X]/1 1; PHOSPHORUS 8 [hp_X]/1 1; PULSATILLA VULGARIS 4 [hp_X]/1 1; THUJA OCCIDENTALIS LEAFY TWIG 6 [hp_X]/1 1
INACTIVE INGREDIENTS: MAGNESIUM STEARATE; MALTODEXTRIN; DEXTROSE

BHI Sinus Tablet

ACTIVE INGREDIENTS

Each tablet contains: *Euphorbium officinarum 6X, *Hydrastis canadensis 6X, Kali bichromicum 6X, Kali iodatum 8X, *Phosphorus 8X, *Pulsatilla 4X, *Thuja occidentalis 6X 42.9 mg each.

*Natural Ingredients

INACTIVE INGREDIENTS

Inactive Ingredients: Dextrose, Magnesium Stearate, Maltodextrin

PURPOSE

Sinus Relief Tablets

Relieves:

• Nasal Congestion

• Sinus Headache & Pressure

• Cold/Flu Nasal Symptoms

USES

For the temporary relief of minor sinus congestion and pressure due to allergic rhinitis and colds

Directions

At first sign of symptoms: Adults and children 4 years and older: 1 tablet every 1/2 to 1 hour until symptoms lessen, then continue with standard dosage.

Standard dosage: Adults and children 4 years and older: Take 1-2 tablet every 4 to 6 hours. Do not exceed 12 tablets in 24 hours. For children under 4, consult your health professional.

Allow tablets to dissolve completely in the mouth, do not swallow.

WARNINGS

If pregnant or breast-feeding, ask a health professional before use. Keep out of reach of children. If symptoms persist or worsen, a health professional should be consulted. Do not use if known sensitivity to BHI Sinus or any of its ingredients exists.

KEEP OUT OF REACH OF CHILDREN

PACKAGE LABEL

Add image transcription here...